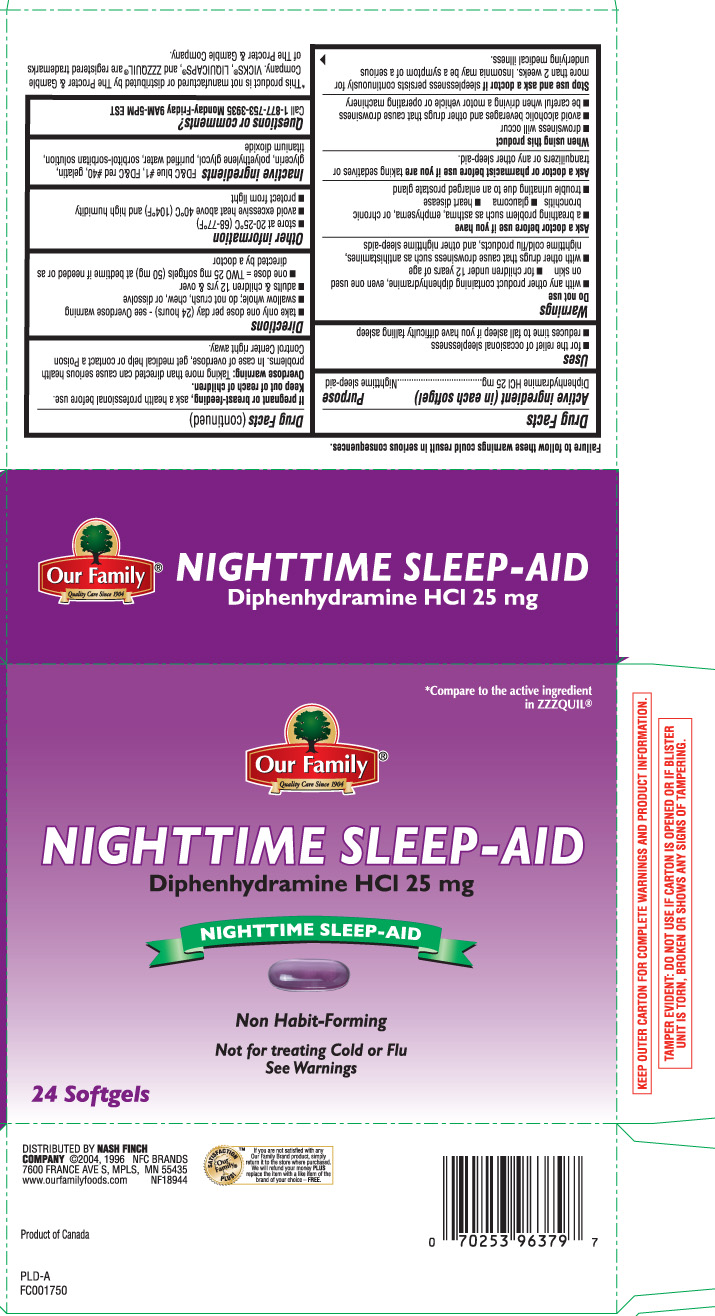 DRUG LABEL: Nighttime Sleep Aid
NDC: 70253-225 | Form: CAPSULE, LIQUID FILLED
Manufacturer: OUR FAMILY (Nash Finch Company)
Category: otc | Type: HUMAN OTC DRUG LABEL
Date: 20131219

ACTIVE INGREDIENTS: DIPHENHYDRAMINE HYDROCHLORIDE 25 mg/1 1
INACTIVE INGREDIENTS: FD&C BLUE NO. 1; GELATIN; GLYCERIN; POLYETHYLENE GLYCOLS; WATER; FD&C RED NO. 40; SORBITOL; TITANIUM DIOXIDE; SORBITAN

Drug Facts

Active ingredient (in each softgel)

Diphenhydramine HCl 25 mg

Purpose

Nighttime sleep-aid

Uses

- for the relief of occasional sleeplessness
- reduces time to fall asleep if you have difficulty falling asleep

Warnings

Do not use

- with any other product containing diphenhydramine, even one used on skin
- for children under 12 years of age
- with other drugs that cause drowsiness such as antihistamines, nighttime cold/flu products, and other nighttime sleep-aids

Ask a doctor before use if you have

- a breathing problem such as asthma, emphysema, or chronic bronchitis
- glaucoma
- heart disease
- trouble urinating due to an enlarged prostate gland

Ask a doctor or pharmacist before use if you are

taking sedatives or tranquilizers or any other sleep-aid.

When using this product

- drowsiness will occur
- avoid alcoholic beverages and other drugs that cause drowsiness
- be careful when driving a motor vehicle or operating machinery

Stop use and ask a doctor if

sleeplessness persists continuously for more than 2 weeks. Insomnia may be a symptom of a serious underlying medical illness.

If pregnant or breast-feeding,

ask a health professional before use.

Keep out of reach of children.

Overdose warning: Taking more than directed can cause serious health problems. In case of overdose, get medical help or contact a Poison Control Center right away.

Directions

- take only one dose per day (24 hours) - see Overdose warning
- swallow whole; do not crush, chew, or dissolve
- adults & children 12 yrs & over
  - one dose = TWO 25 mg softgels (50 mg) at bedtime if needed or as directed by a doctor

Other information

- store at 20-25°C (68-77°F)
- avoid excessive heat above 40°C (104°F) and high humidity
- protect from light

Inactive ingredients

FD&C blue #1, FD&C red #40, gelatin, glycerin, polyethylene glycol, purified water, sorbitol-sorbitan solution, titanium dioxide

Questions or comments?

Call 1-877-753-3935 Monday-Friday 9AM-5PM EST

Principal Display Panel

*Compare to the active ingredient in ZZZQUIL®

NIGHTTIME SLEEP-AID

Diphenhydramine HCl 25 mg

Nighttime Sleep-Aid

Non Habit-Forming

Not for treating Cold or Flu

See Warnings

Softgels

DISTRIBUTED BY NASH FINCH COMPANY

7600 FRANCE AVE S, MPLS, MN 55435

www.ourfamilyfoods.com

Product of Canada

Failure to follow these warnings could result in serious consequences.

KEEP OUTER CARTON FOR COMPLETE WARNINGS AND PRODUCT INFORMATION.

TAMPER EVIDENT: DO NOT USE IF CARTON IS OPENED OR IF BLISTER UNIT IS TORN, BROKEN OR SHOWS ANY SIGNS OF TAMPERING.

*This product is not manufactured or distributed by The Procter & Gamble Company. VICKS®, LIQUICAPS®, and ZZZQUIL® are registered trademarks of The Procter & Gamble Company.

Package Label

Our Family Nighttime Sleep Aid Softgel